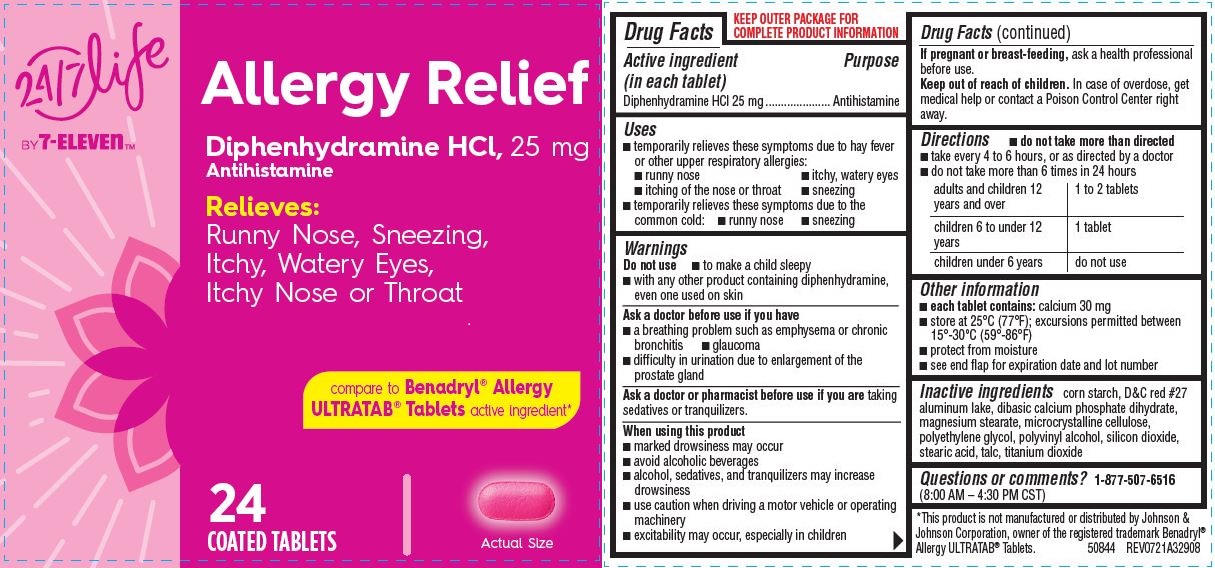 DRUG LABEL: Allergy Relief, 24-7 Lift by 7-Eleven
NDC: 66715-6514 | Form: TABLET, COATED
Manufacturer: Lil' Drug Store products, Inc.
Category: otc | Type: HUMAN OTC DRUG LABEL
Date: 20241216

ACTIVE INGREDIENTS: DIPHENHYDRAMINE HYDROCHLORIDE 25 mg/1 1
INACTIVE INGREDIENTS: MAGNESIUM STEARATE; TITANIUM DIOXIDE; D&C RED NO. 27 ALUMINUM LAKE; DIBASIC CALCIUM PHOSPHATE DIHYDRATE; POLYVINYL ALCOHOL, UNSPECIFIED; TALC; STARCH, CORN; POLYETHYLENE GLYCOL, UNSPECIFIED; SILICON DIOXIDE; MICROCRYSTALLINE CELLULOSE; STEARIC ACID

Allergy Relief, 24 ct, 24/7 Life by 7-ElevenTM

Drug Facts

Active ingredient

Active ingredient (in each tablet)
Diphenhydramine HCl 25 mg

Purpose

Antihistamine

Uses

- temporarily relieves these symptoms due to hay fever or other upper respiratory allergies:
- runny nose
- itchy, watery eyes
- itching of the nose or throat
- sneezing
- temporarily relieves these symptoms due to the common cold:
- runny nose
- sneezing

Warnings

Do not use

- to make a child sleepy
- with any other product containing diphenhydramine, even one used on skin

Ask a doctor before use if you have

- a breathing problem such as emphysema or chronic bronchitis
- glaucoma
- difficulty in urination due to enlargement of the prostate gland

Ask a doctor or pharmacist before use if you are taking sedatives or tranquilizers.

When using this product

- marked drowsiness may occur
- avoid alcoholic beverages
- alcohol, sedatives, and tranquilizers may increase drowsiness
- use caution when driving a motor vehicle or operating machinery
- excitability may occur, especially in children

If pregnant or breast-feeding, ask a health professional before use.

Keep out of reach of children. In case of overdose, get medical help or contact a Poison Control Center right away.

Directions

- do not take more than directed
- take every 4 to 6 hours, or as directed by a doctor
- do not take more than 6 times in 24 hours
  adults and children 12 years and over | 1 to 2 tablets
  children 6 to under 12 years | 1 tablet
  children under 6 years | do not use

Other information

- each tablet contains: calcium 30 mg
- store at 25°C (77°F); excursions permitted between 15°-30°C (59°-86°F)
- protect from moisture
- see end flap for expiration date and lot number

Inactive ingredients

corn starch, D&C red #27 aluminum lake, dibasic calcium phosphate dihydrate, magnesium stearate, microcrystalline cellulose, polyethylene glycol, polyvinyl alcohol, silicon dioxide, stearic acid, talc, titanium dioxide

Questions or comments? 1-877-507-6516 (8:00 AM – 4:30 PM CST)

Allergy Relief 24ct, 24/7 Life by 7-ElevenTM

Allergy Relief
Diphenhydramine HCl, 25 mg
Antihistamine
Relieves:
Runny Nose, Sneezing,
Itchy, Watery Eyes,
Itchy Nose or Throat

compare to Benadryl® Allergy
ULTRATAB® Tablets active ingredient*

24

COATED TABLETS

[tablet image]

Actual Size